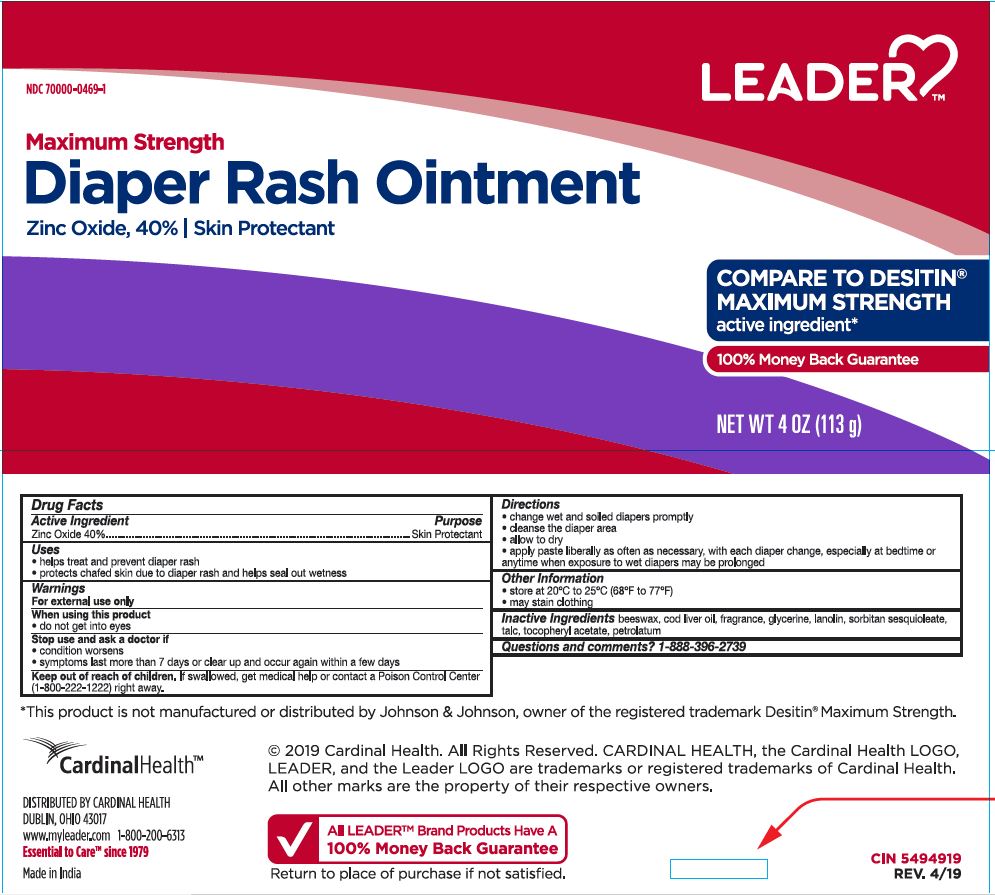 DRUG LABEL: Zinc Oxide 40%
NDC: 70000-0469 | Form: OINTMENT
Manufacturer: Cardinal Health
Category: otc | Type: HUMAN OTC DRUG LABEL
Date: 20251125

ACTIVE INGREDIENTS: ZINC OXIDE 40 g/100 g
INACTIVE INGREDIENTS: LANOLIN; GLYCERIN; YELLOW WAX; PETROLATUM; COD LIVER OIL; TALC; SORBITAN SESQUIOLEATE; .ALPHA.-TOCOPHEROL ACETATE

CR-1189 Zinc Oxide 40% NDC 70000-0469-1

Active Ingredient

Zinc oxide 40%

Purpose

Skin Protectant

Uses

- helps treat and prevent diaper rash
- protects chafed skin due to diaper rash and helps seal out wetness

Warnings

For external use only

When using this product

do not get into eyes

Stop use and ask a doctor if

- condition worsens.
- symptoms last more than 7 days or clear up and occur again within a few days

KEEP OUT OF REACH OF CHILDREN

If swallowed, get medical help or contact a Poison Control Center (1-800-222-1222) right away.

Directions

- change wet and soiled diapers promptly
- cleanse the diaper area
- allow to dry
- apply paste liberally as often as necessary, with each diaper change, especially at bedtime or anytime when exposure to wet diapers may be prolonged

Other Information

- store at 20°C to 25°C (68°F to 77°F)
- may stain clothing

Inactive Ingredients

beeswax, cod liver oil, fragrance, glycerine, lanolin, sorbitan sesquioleate, talc, tocopheryl acetate, petrolatum

Questions and comments?

1-888-396-2739